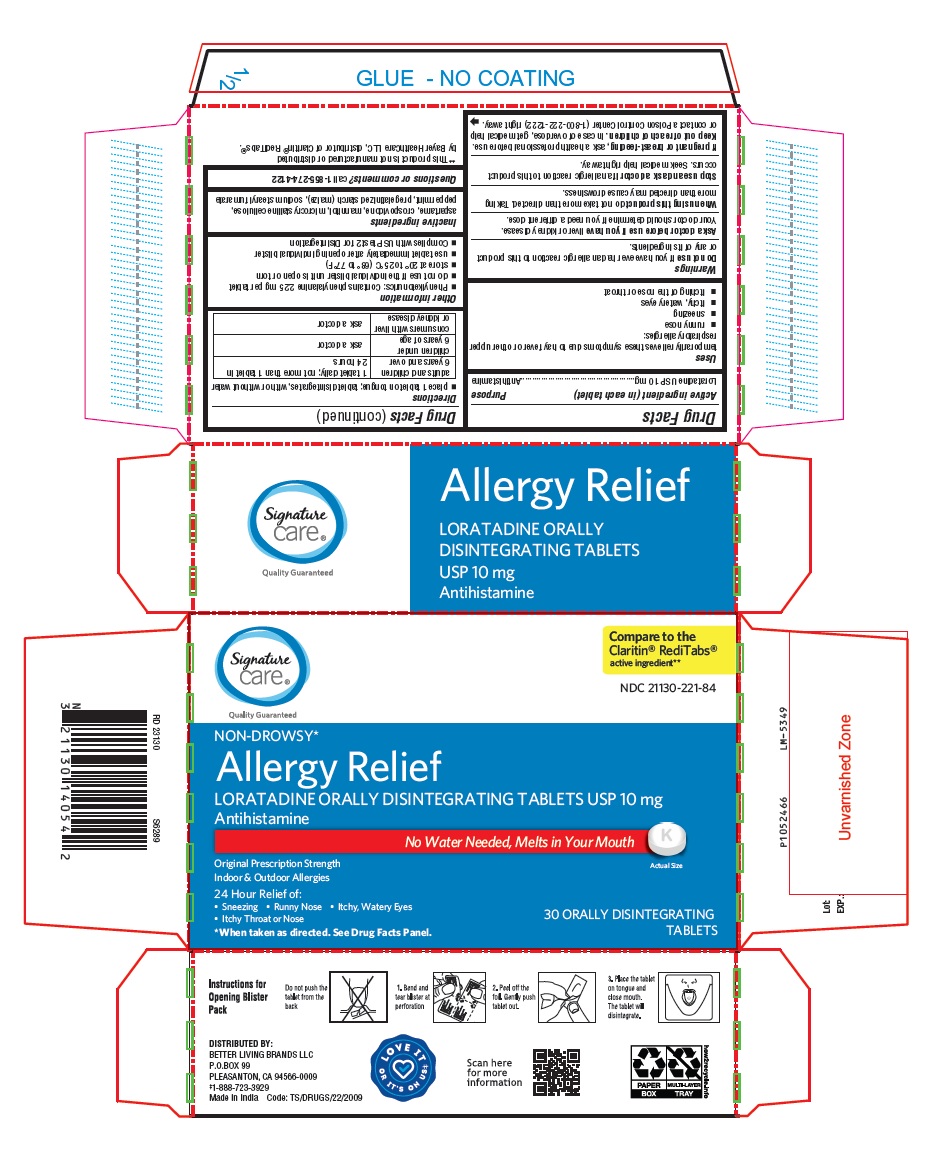 DRUG LABEL: Loratadine ODT
NDC: 21130-221 | Form: TABLET, ORALLY DISINTEGRATING
Manufacturer: Better Living Brands, LLC
Category: otc | Type: Human OTC Drug Label
Date: 20230925

ACTIVE INGREDIENTS: LORATADINE 10 mg/1 1
INACTIVE INGREDIENTS: ASPARTAME; CROSPOVIDONE (120 .MU.M); MANNITOL; MICROCRYSTALLINE CELLULOSE; PEPPERMINT; STARCH, CORN; SODIUM STEARYL FUMARATE

Loratadine Orally Disintegrating Tablets USP 10 mg

Active ingredient (in each tablet)

Loratadine USP 10 mg

Purpose

Antihistamine

Uses

temporarily relieves these symptoms due to hay fever or other upper respiratory allergies:

- runny nose
- sneezing
- itchy, watery eyes
- itching of the nose or throat

Do not use

if you have ever had an allergic reaction to this product or any of its ingredients.

Ask a doctor before use if you have

liver or kidney disease. Your doctor should determine if you need a different dose.

When using this product

do not take more than directed. Taking more than directed may cause drowsiness.

Stop use and ask a doctor if

an allergic reaction to this product occurs. Seek medical help right away.

If pregnant or breast-feeding,

ask a health professional before use.

Keep out of reach of children.

In case of overdose, get medical help or contact a Poison Control Center (1-800-222-1222) right away.

Directions

- place 1 tablet on tongue; tablet disintegrates, with or without water

adults and children 6 years and over | 1 tablet daily; not more than 1 tablet in 24 hours
children under 6 years of age | ask a doctor
consumers with liver or kidney disease | ask a doctor

Other information

- Phenylketonurics: Contains phenylalanine 2.25 mg per tablet
- do not use if the individual blister unit is open or torn
- store at 20° to 25°C (68° to 77°F)
- use tablet immediately after opening individual blister
- Complies with USP test 2 for Disintegration

Inactive ingredients

aspartame, crospovidone, mannitol, microcrystalline cellulose, peppermint, pregelatinized starch (maize), sodium stearyl fumarate

Questions or comments?

call 1-855-274-4122
DISTRIBUTED BY:
BETTER LIVING BRANDS LLC
P.O.BOX 99
PLEASANTON, CA 94566-0009
‡1-888-723-3929
Made in India
Code: TS/DRUGS/22/2009

PACKAGE LABEL-PRINCIPAL DISPLAY PANEL - 10 mg, Blister Carton 30 (3 X 10) Orally Disintegrating Tablets

Signature
care®
Quality Guaranteed
Compare to the
Claritin® RediTabs®
active ingredient**
NDC 21130-221-84
NON-DROWSY*
Allergy Relief
LORATADINE ORALLY DISINTEGRATING TABLETS USP 10 mg
Antihistamine
No Water Needed, Melts in Your Mouth
Original Prescription Strength
Indoor & Outdoor Allergies
24 Hour Relief of:

- Sneezing
- Runny Nose
- Itchy, Watery Eyes
- Itchy Throat or Nose

*When taken as directed. See Drug Facts Panel.
Actual Size
30 ORALLY DISINTEGRATING
TABLETS